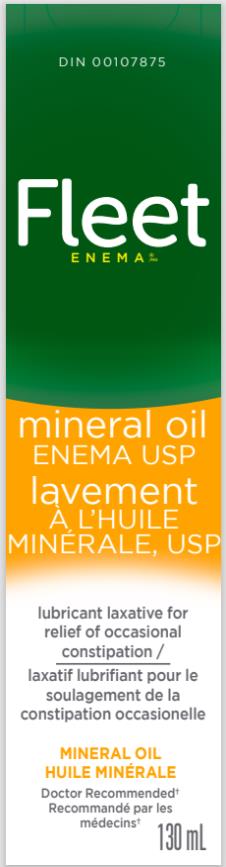 DRUG LABEL: FLEET
NDC: 0132-0556 | Form: ENEMA
Manufacturer: C.B. Fleet Company, Inc.
Category: otc | Type: HUMAN OTC DRUG LABEL
Date: 20240506

ACTIVE INGREDIENTS: MINERAL OIL 100 g/100 mL

Fleet Enema, Mineral Oil, Canada 0132-0556-40

Fleet Mineral Oil

Drug Facts

Active ingredient

Mineral oil (Heavy) 130 mL

Purpose

Lubricant laxative

Uses

- relieves occasional constipation
- softens the stool

Warnings

Do not use

with any other laxative.

Ask a doctor or pharmacist before use if you have

- abdominal pain
- nausea or vomiting
- fever
- noticed a sudden change in bowel habits lasting for longer than 2 weeks
- are pregnant or breastfeeding

When using this product

- do not take it within 2 hours of other medicines
- it may take 2 to 15 minutes to have a bowel movement
- overuse or extended use may cause dependence for bowel function

Stop use and ask a doctor if

- rectal bleeding occurs
- symptoms last for more than 7 days.

This may be a sign of serious condition.

Inactive

- None

Other warnings

- overuse or extended use may cause dependence for bowel function
- do not give to infants or children under 12 years, or to bedridden or aged patients, unless directed by a doctor

Keep out of reach of children.

In case of overdose, call a poison control centre or get medical help right away.

Directions

- Adults and children 12 years and older; take 120 mL as a single dose
- Do not take more than 120 mL in 24 hours

Other information

store at room temperature

Questions?

Call 1-866-255-6960

PRINCIPAL DISPLAY PANEL

Fleet®

Mineral Oil
Enema

130 mL